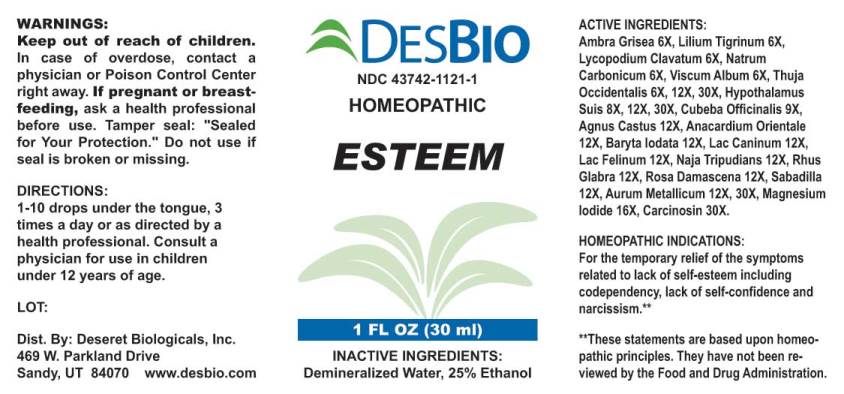 DRUG LABEL: Esteem
NDC: 43742-1121 | Form: LIQUID
Manufacturer: Deseret Biologicals, Inc.
Category: homeopathic | Type: HUMAN OTC DRUG LABEL
Date: 20240131

ACTIVE INGREDIENTS: AMBERGRIS 6 [hp_X]/1 mL; LILIUM LANCIFOLIUM WHOLE FLOWERING 6 [hp_X]/1 mL; LYCOPODIUM CLAVATUM SPORE 6 [hp_X]/1 mL; SODIUM CARBONATE 6 [hp_X]/1 mL; VISCUM ALBUM FRUITING TOP 6 [hp_X]/1 mL; THUJA OCCIDENTALIS LEAFY TWIG 6 [hp_X]/1 mL; SUS SCROFA HYPOTHALAMUS 8 [hp_X]/1 mL; PIPER CUBEBA FRUIT 9 [hp_X]/1 mL; CHASTE TREE 12 [hp_X]/1 mL; SEMECARPUS ANACARDIUM JUICE 12 [hp_X]/1 mL; BARIUM IODIDE 12 [hp_X]/1 mL; CANIS LUPUS FAMILIARIS MILK 12 [hp_X]/1 mL; FELIS CATUS MILK 12 [hp_X]/1 mL; NAJA NAJA VENOM 12 [hp_X]/1 mL; RHUS GLABRA TOP 12 [hp_X]/1 mL; ROSA X DAMASCENA FLOWERING TOP 12 [hp_X]/1 mL; SCHOENOCAULON OFFICINALE SEED 12 [hp_X]/1 mL; GOLD 12 [hp_X]/1 mL; MAGNESIUM IODIDE 16 [hp_X]/1 mL; HUMAN BREAST TUMOR CELL 30 [hp_X]/1 mL
INACTIVE INGREDIENTS: WATER; ALCOHOL

Drug Facts:

ACTIVE INGREDIENTS:

Ambra Grisea 6X, Lilium Tigrinum 6X, Lycopodium Clavatum 6X, Natrum Carbonicum 6X, Viscum Album 6X, Thuja Occidentalis 6X, 12X, 30X, Hypothalamus Suis 8X, 12X, 30X, Cubeba Officinalis 9X, Agnus Castus 12X, Anacardium Orientale 12X, Baryta Iodata 12X, Lac Caninum 12X, Lac Felinum 12X, Naja Tripudians 12X, Rhus Glabra 12X, Rosa Damascena 12X, Sabadilla 12X, Aurum Metallicum 12X, 30X, Magnesium Iodide 16X, Carcinosin 30X.

HOMEOPATHIC INDICATIONS:

For the temporary relief of the symptoms related to lack of self-esteem including codependency lack of self-confidence and narcissism.**

**These statements are based upon traditional homeopathic principles. They have not been reviewed by the Food and Drug Administration.

WARNINGS:

Keep out of reach of children. In case of overdose, contact physician or a Poison Control Center right away.

If pregnant or breast-feeding, ask a health professional before use.

Tamper seal: "Sealed for Your Protection." Do not use if seal is broken or missing.

Keep out of reach of children. In case of overdose, contact physician or a Poison Control Center right away.

DIRECTIONS:

1-10 drops under the tongue, 3 times a day or as directed by a health professional. Consult a physician for use in children under 12 years of age.

HOMEOPATHIC INDICATIONS:

For the temporary relief of the symptoms related to lack of self-esteem including codependency lack of self-confidence and narcissism.**

**These statements are based upon traditional homeopathic principles. They have not been reviewed by the Food and Drug Administration.

INACTIVE INGREDIENTS:

Demineralized Water, 25% Ethanol

QUESTIONS:

Dist. By: Deseret Biologicals, Inc.

469 W. Parkland Drive

Sandy, UT 84070 www.desbio.com

PACKAGE LABEL DISPLAY:

DESBIO
NDC 43742-1121-1
HOMEOPATHIC
ESTEEM
1 FL OZ (30 ml)